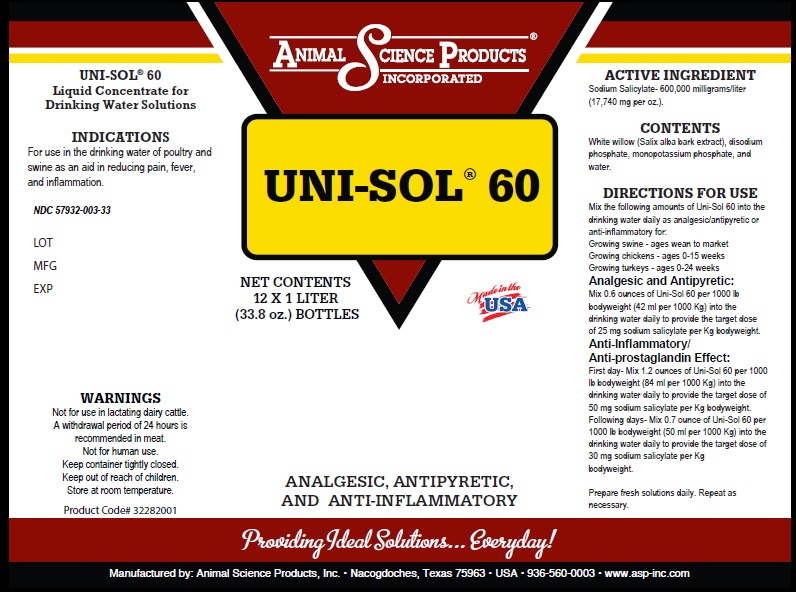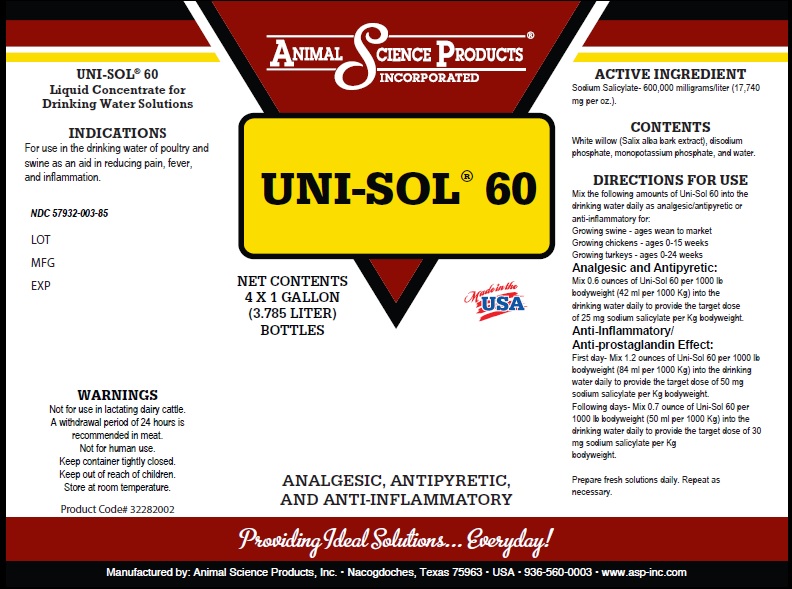 DRUG LABEL: UNI-SOL 60
NDC: 57932-003 | Form: SOLUTION
Manufacturer: Animal Science Products Inc
Category: animal | Type: OTC ANIMAL DRUG LABEL
Date: 20251028

ACTIVE INGREDIENTS: SODIUM SALICYLATE 600000 mg/1 L
INACTIVE INGREDIENTS: WATER; SALIX ALBA BARK; SODIUM PHOSPHATE, DIBASIC, ANHYDROUS; POTASSIUM PHOSPHATE, MONOBASIC

UNI-SOL® 60
Liquid Concentrate for Drinking Water Solutions

Ingredients

Active ingredient: Sodium Salicylate- 600,000 milligrams/liter (17,740 mg per oz.).

Directions for Use

Mix the following amounts of Uni-Sol 60 into the drinking water daily as analgesic/antipyretic or anti-inflammatory for:
Growing swine - ages wean to market
Growing chickens - ages 0-15 weeks
Growing turkeys - ages 0-24 weeks

Analgesic and Antipyretic:
Mix 0.6 ounces of Uni-Sol 60 per 1000 lb bodyweight (42 ml per 1000 Kg) into the drinking water daily to provide the target dose of 25 mg sodium salicylate per Kg bodyweight.

Anti-Inflammatory/ Anti-prostaglandin Effect:

First day- Mix 1.2 ounces of Uni-Sol 60 per 1000 lb bodyweight (84 ml per 1000 Kg) into the drinking water daily to provide the target dose of 50 mg sodium salicylate per Kg bodyweight. Following days- Mix 0.7 ounce of Uni-Sol 60 per 1000 lb bodyweight (50 ml per 1000 Kg) into the drinking water daily to provide the target dose of 30 mg sodium salicylate per Kg bodyweight.

Prepare fresh solutions daily. Repeat as necessary.

Indications

For use in the drinking water of poultry and swine as an

PURPOSE

aid in reducing pain, fever and inflammation

Warnings

Not for use in lactating dairy cattle.
A withdrawal period of 24 hours is recommended in meat.
Not for human use.
Keep container tightly closed.
Keep out of reach of children.
Store at room temperature.

Excipients

White willow (Salix alba bark extract), disodium phosphate,
monopotassium phosphate, and water.

Product Labeling

UNI-SOL 60

Net Contents 33.8 oz (1 Liter)

Net Contents 1 Gallon (3.785 Liter)

Analgesic, Antipyretic, and Anti-Inflammatory

Providing Ideal Solutions.. Everyday!

Manufactured by Animal Science Products, Inc - Nacogdoches, Texas 75963 - USA - 936-560-0003 - www.asp-inc.com